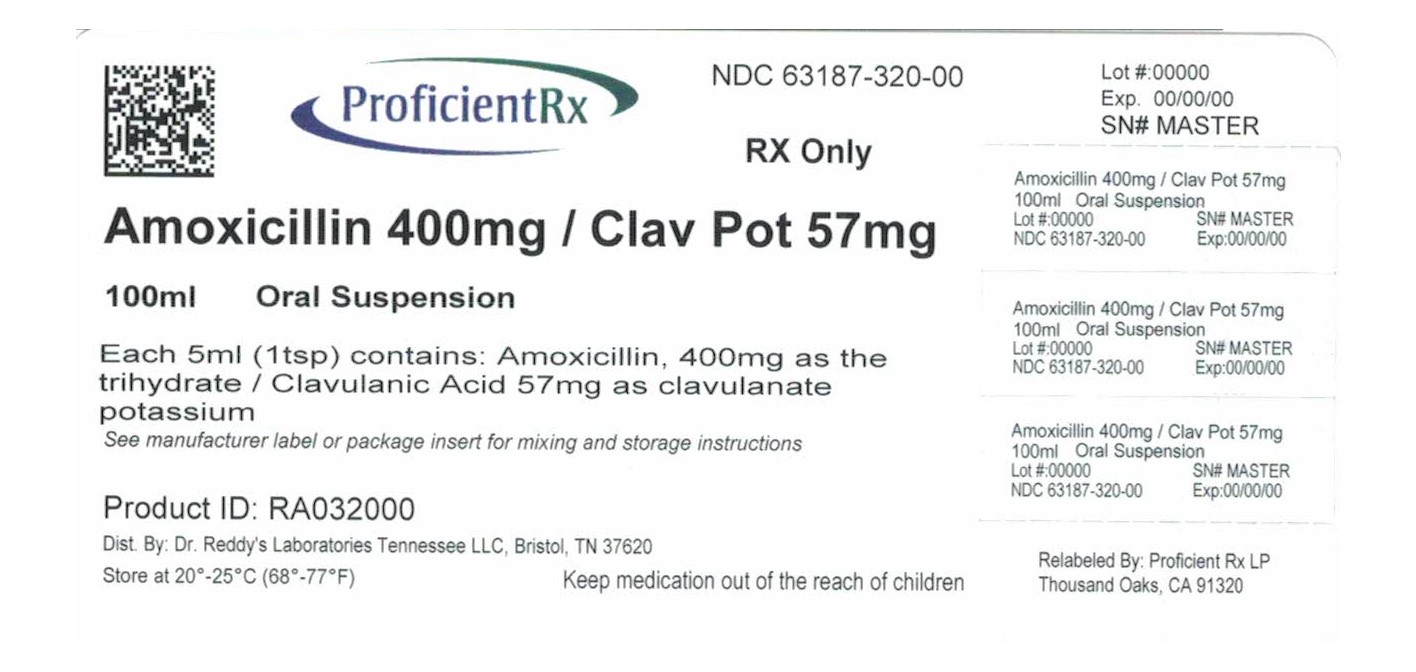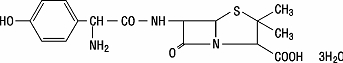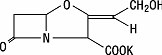 DRUG LABEL: amoxicillin and clavulanate potassium
NDC: 63187-320 | Form: POWDER, FOR SUSPENSION
Manufacturer: Proficient Rx LP
Category: prescription | Type: HUMAN PRESCRIPTION DRUG LABEL
Date: 20191101

ACTIVE INGREDIENTS: AMOXICILLIN 400 mg/5 mL; CLAVULANATE POTASSIUM 57 mg/5 mL
INACTIVE INGREDIENTS: SILICON DIOXIDE; XANTHAN GUM; ASPARTAME; HYPROMELLOSE, UNSPECIFIED; MANNITOL; SACCHARIN SODIUM

HIGHLIGHTS OF PRESCRIBING INFORMATION

These highlights do not include all the information needed to use Amoxicillin and Clavulanate Potassium safely and effectively. See full prescribing information for Amoxicillin and Clavulanate Potassium.
Amoxicillin and Clavulanate Potassium Tablets, Powder for Oral Suspension and Chewable Tablets
Initial U.S. Approval: 1984
To reduce the development of drug-resistant bacteria and maintain the effectiveness of Amoxicillin and Clavulanate Potassium and other antibacterial drugs, Amoxicillin and Clavulanate Potassium should be used only to treat infections that are proven or strongly suspected to be caused by bacteria.

1 INDICATIONS AND USAGE

Amoxicillin and Clavulanate Potassium is a combination penicillin-class antibacterial and beta‑lactamase inhibitor indicated for treatment of the following:

Lower respiratory tract infections (1.1)

Acute bacterial otitis media (1.2)

Sinusitis (1.3)

Skin and skin structure infections (1.4)

Urinary tract infections (1.5)

2 DOSAGE AND ADMINISTRATION

- Adults and Pediatric Patients > 40 kg: 500 or 875 mg every 12 hours or 250 or 500 mg every 8 hours. (2.1, 2.2)
- Pediatric patients aged 12 weeks (3 months) and older: 25 to 45 mg/kg/day every 12 hours or 20 to 40 mg/kg/day every 8 hours, up to the adult dose. (2.2)
- Neonates and infants < 12 weeks of age: 30 mg/kg/day divided every 12 hours, based on the amoxicillin component. Use of the 125 mg/5 mL oral suspension is recommended. (2.2)

3 DOSAGE FORMS AND STRENGTHS

Formulations and amoxicillin/clavulanate content are:

Tablets: 250 mg/125 mg, 500 mg/125 mg, 875 mg/125 mg; 875 mg/125 mg tablets are scored. (3)

Powder for Oral Suspension: 125 mg/31.25 mg per 5 mL, 200 mg/28.5 mg per 5 mL, 250 mg/62.5 mg per 5 mL, 400 mg/57 mg per 5 mL (3)

Chewable Tablets: 125 mg/31.25 mg, 200 mg/28.5 mg, 250 mg/62.5 mg, 400 mg/57 mg (3)

4 CONTRAINDICATIONS

- History of a serious hypersensitivity reaction (e.g., anaphylaxis or Stevens-Johnson syndrome) to Amoxicillin and Clavulanate Potassium or to other beta‑lactams (e.g., penicillins or cephalosporins) (4)
- History of cholestatic jaundice/hepatic dysfunction associated with Amoxicillin and Clavulanate Potassium . (4)

5 WARNINGS AND PRECAUTIONS

- Serious (including fatal) hypersensitivity reactions: Discontinue Amoxicillin and Clavulanate Potassium if a reaction occurs. (5.1)
- Hepatic dysfunction and cholestatic jaundice: Discontinue if signs/symptoms of hepatitis occur. Monitor liver function tests in patients with hepatic impairment. (5.2)
- Clostridium difficile-associated diarrhea (CDAD): Evaluate patients if diarrhea occurs. (5.3)
- Patients with mononucleosis who receive Amoxicillin and Clavulanate Potassium develop skin rash. Avoid Amoxicillin and Clavulanate Potassium use in these patients. (5.4)
- Overgrowth: The possibility of superinfections with fungal or bacterial pathogens should be considered during therapy. (5.5)

6 ADVERSE REACTIONS

The most frequently reported adverse effects were diarrhea/loose stools (9%), nausea (3%), skin rashes and urticaria (3%),vomiting (1%) and vaginitis (1%) (6.1)

To report SUSPECTED ADVERSE REACTIONS, contact Dr. Reddy’s Laboratories Inc., at 1-888-375-3784 or FDA at 1-800-FDA-1088 or www.fda.gov/medwatch.

7 DRUG INTERACTIONS

- Co‑administration with probenecid is not recommended. (7.1)
- Concomitant use of Amoxicillin and Clavulanate Potassium and oral anticoagulants may increase the prolongation of prothrombin time. (7.2)
- Coadministration with allopurinol increases the risk of rash. (7.3)
- Amoxicillin and Clavulanate Potassium may reduce efficacy of oral contraceptives. (7.4)

8 USE IN SPECIFIC POPULATIONS

- Pediatric Use: Modify dose in patients 12 weeks or younger. (8.4)
- Renal impairment; Dosage adjustment is recommended for severe renal impairment (GFR< 30mL/min). (2.3, 8.6)

FULL PRESCRIBING INFORMATION

1 INDICATIONS AND USAGE

To reduce the development of drug‑resistant bacteria and maintain the effectiveness of Amoxicillin and Clavulanate Potassium and other antibacterial drugs, Amoxicillin and Clavulanate Potassium should be used only to treat infections that are proven or strongly suspected to be caused by susceptible bacteria. When culture and susceptibility information are available, they should be considered in selecting or modifying antibacterial therapy. In the absence of such data, local epidemiology and susceptibility patterns may contribute to the empiric selection of therapy.

Amoxicillin and Clavulanate Potassium is a combination penicillin-class antibacterial and beta-lactamase inhibitor indicated in the treatment of infections due to susceptible isolates of the designated bacteria in the conditions listed below*:

1.1 Lower Respiratory Tract Infections

caused by beta‑lactamase–producing isolates of Haemophilus influenzae and Moraxella catarrhalis.

1.2 Acute Bacterial Otitis Media

caused by beta‑lactamase–producing isolates of H. influenzae and M. catarrhalis.

1.3 Sinusitis

caused by beta‑lactamase–producing isolates of H. influenzae and M. catarrhalis.

1.4 Skin and Skin Structure Infections

caused by beta‑lactamase–producing isolates of Staphylococcus aureus, Escherichia coli, and Klebsiella species.

1.5 Urinary Tract Infections

caused by beta‑lactamase–producing isolates of E. coli, Klebsiella species, and Enterobacter species.

1.6 Limitations of Use

When susceptibility test results show susceptibility to amoxicillin, indicating no beta-lactamase production, Amoxicillin and Clavulanate Potassium should not be used.

2 DOSAGE AND ADMINISTRATION

Amoxicillin and Clavulanate Potassium may be taken without regard to meals; however, absorption of clavulanate potassium is enhanced when Amoxicillin and Clavulanate Potassium is administered at the start of a meal. To minimize the potential for gastrointestinal intolerance, Amoxicillin and Clavulanate Potassium should be taken at the start of a meal.

2.1 Adults

The usual adult dose is one 500-mg tablet of Amoxicillin and Clavulanate Potassium every 12 hours or one 250-mg tablet of Amoxicillin and Clavulanate Potassium every 8 hours. For more severe infections and infections of the respiratory tract, the dose should be one 875-mg tablet of Amoxicillin and Clavulanate Potassium every 12 hours or one 500-mg tablet of Amoxicillin and Clavulanate Potassium every 8 hours. Adults who have difficulty swallowing may be given the 125 mg/5 mL or 250 mg/5 mL suspension in place of the 500-mg tablet. The 200 mg/5 mL suspension or the 400 mg/5 mL suspension may be used in place of the 875-mg tablet.

Two 250-mg tablets of Amoxicillin and Clavulanate Potassium should not be substituted for one 500-mg tablet of Amoxicillin and Clavulanate Potassium. Since both the 250-mg and 500-mg tablets of Amoxicillin and Clavulanate Potassium contain the same amount of clavulanic acid (125 mg, as the potassium salt), two 250-mg tablets are not equivalent to one 500-mg tablet of Amoxicillin and Clavulanate Potassium.

The 250-mg tablet of Amoxicillin and Clavulanate Potassium and the 250-mg chewable tablet should not be substituted for each other, as they are not interchangeable. The 250-mg tablet of Amoxicillin and Clavulanate Potassium and the 250-mg chewable tablet do not contain the same amount of clavulanic acid (as the potassium salt). The 250-mg tablet of Amoxicillin and Clavulanate Potassium contains 125 mg of clavulanic acid, whereas the 250-mg chewable tablet contains 62.5 mg of clavulanic acid.

2.2 Pediatric Patients

Based on the amoxicillin component, Amoxicillin and Clavulanate Potassium should be dosed as follows:

Neonates and Infants Aged <12 weeks (<3 months): The recommended dose of Amoxicillin and Clavulanate Potassium is 30 mg/kg/day divided every 12 hours, based on the amoxicillin component. Experience with the 200 mg/5 mL formulation in this age group is limited, and thus, use of the 125 mg/5 mL oral suspension is recommended.

Patients Aged 12 weeks (3 months) and Older: See dosing regimens provided in Table 1. The every 12 hour regimen is recommended as it is associated with significantly less diarrhea [see Clinical Studies (14.2)]. However, the every 12 hour suspension (200 mg/5 mL and 400 mg/5 mL) and chewable tablets (200 mg and 400 mg) contain aspartame and should not be used by phenylketonurics. [see Warnings and Precautions (5.6)]

Table 1: Dosing in Patients Aged 12 weeks (3 months) and Older

INFECTION | DOSING REGIMEN
INFECTION | Every 12 hours | Every 8 hours
INFECTION | 200 mg/5 mL or 400 mg/5 mL oral suspensiona | 125 mg/5 mL or 250 mg/5 mL oral suspensiona
Otitis mediab, sinusitis, lower respiratory tract infections, and more severe infections | 45 mg/kg/day every 12 hours | 40 mg/kg/day every 8 hours
Less severe infections | 25 mg/kg/day every 12 hours | 20 mg/kg/day every 8 hours

a Each strength of suspension of Amoxicillin and Clavulanate Potassium is available as a chewable tablet for use by older children.

b Duration of therapy studied and recommended for acute otitis media is 10 days.

Patients Weighing 40 kg or More: Pediatric patients weighing 40 kg or more should be dosed according to adult recommendations.

The 250-mg tablet of Amoxicillin and Clavulanate Potassium should not be used until the child weighs at least 40 kg,due to the different amoxicillin to clavulanic acid ratios in the 250-mg tablet of Amoxicillin and Clavulanate Potassium (250/125) versus the 250-mg chewable tablet of Amoxicillin and Clavulanate Potassium (250/62.5).

2.3 Patients with Renal Impairment

Patients with impaired renal function do not generally require a reduction in dose unless the impairment is severe. Renal impairment patients with a glomerular filtration rate of <30 mL/min should not receive the 875‑mg dose. Patients with a glomerular filtration rate of 10 to 30 mL/min should receive 500 mg or 250 mg every 12 hours, depending on the severity of the infection. Patients with a glomerular filtration rate less than 10 mL/min should receive 500 mg or 250 mg every 24 hours, depending on severity of the infection.

Hemodialysis patients should receive 500 mg or 250 mg every 24 hours,depending on severity of the infection. They should receive an additional dose both during and at the end of dialysis.

2.4 Directions for Mixing Oral Suspension

Prepare a suspension at time of dispensing as follows: Tap bottle until all the powder flows freely. Add approximately 2/3 of the total amount of water for reconstitution (see Table 2 below) and shake vigorously to suspend powder. Add remainder of the water and again shake vigorously.

Table 2: Amount of Water for Mixing Oral Suspension

Strength | Bottle Size | Amount of Waterfor Reconstitution | Contents of EachTeaspoonful (5 mL)
125 mg/5 mL | 75 mL100 mL150 mL | 67 mL90 mL134 mL | 125 mg amoxicillin and 31.25 mg of clavulanic acid as the potassium salt
200 mg/5 mL | 50 mL75 mL100 mL | 50 mL75 mL95 mL | 200 mg amoxicillin and 28.5 mg of clavulanic acid as the potassium salt
250 mg/5 mL | 75 mL100 mL150 mL | 65 mL87 mL130 mL | 250 mg amoxicillin and 62.5 mg of clavulanic acid as the potassium salt
400 mg/5 mL | 50 mL75 mL100 mL | 50 mL70 mL90 mL | 400 mg amoxicillin and 57.0 mg of clavulanic acid as the potassium salt

Note: Shake oral suspension well before using. Reconstituted suspension must be stored under refrigeration and discarded after 10 days.

3 DOSAGE FORMS AND STRENGTHS

Tablets:

- 250‑mg/125-mg Tablets: Each white oval film-coated tablet, debossed with AUGMENTIN on one side and 250/125 on the other side, contains 250 mg of amoxicillin and 125 mg clavulanic acid as the potassium salt.
- 500‑mg/125-mg Tablets: Each white oval film-coated tablet, debossed with AUGMENTIN on one side and 500/125 on the other side, contains 500 mg amoxicillin and 125 mg of clavulanic acid as the potassium salt.
- 875‑mg/125-mg Tablets: Each scored white capsule‑shaped tablet, debossed with AUGMENTIN 875 on one side and scored on the other side, contains 875 mg amoxicillin and 125 mg clavulanic acid as the potassium salt.

Powder for Oral Suspension:

- 125 mg/31.25 mg per 5 mL: Banana-flavored powder for oral suspension (each 5 mL of reconstituted suspension contains 125 mg amoxicillin and 31.25 mg of clavulanic acid as the potassium salt).
- 200 mg/28.5 mg per 5 mL: Orange-favored powder for oral suspension (each 5 mL of reconstituted suspension contains 200 mg amoxicillin and 28.5 mg of clavulanic acid as the potassium salt).
- 250 mg/62.5 mg per 5 mL: Orange-flavored powder for oral suspension (each 5 mL of reconstituted suspension contains 250 mg amoxicillin and 62.5 mg of clavulanic acid as the potassium salt).
- 400 mg/57 mg per 5 mL Orange-flavored powder for oral suspension (each 5 mL of reconstituted suspension contains 400 mg amoxicillin and 57.0 mg of clavulanic acid as the potassium salt).

Chewable Tablets:

- 125-mg/31.25-mg Chewable Tablets: Each mottled yellow, round, lemon-lime-flavored tablet, debossed with BMP 189 contains 125 mg amoxicillin and 31.25 mg clavulanic acid as the potassium salt.
- 200-mg/28.5 mg Chewable Tablets: Each mottled pink, round, biconvex cherry-banana-flavored tablet, debossed with PL over C20 contains 200 mg amoxicillin and 28.5 mg clavulanic acid as the potassium salt.
- 250-mg/62.5-mg Chewable Tablets: Each mottled yellow, round, lemon-lime-flavored tablet, debossed with BMP 190 contains 250 mg amoxicillin and 62.5 mg clavulanic acid as the potassium salt.
- 400-mg/57-mg Chewable Tablets: Each mottled pink, round, biconvex cherry-banana-flavored tablet, debossed with PL over C40 contains 400 mg amoxicillin and 57.0 mg clavulanic acid as the potassium salt.

The 250-mg tablet of Amoxicillin and Clavulanate Potassium and the 250-mg chewable tablet should NOT be substituted for each other, as they are not interchangeable and the 250-mg tablet should not be used in children weighing less than 40 kg. The 250-mg tablet of Amoxicillin and Clavulanate Potassium and the 250-mg chewable tablet do not contain the same amount of clavulanic acid. The 250-mg tablet of Amoxicillin and Clavulanate Potassium contains 125 mg of clavulanic acid whereas the 250-mg chewable tablet contains 62.5 mg of clavulanic acid.

Two 250 mg tablets of Amoxicillin and Clavulanate Potassium should NOT be substituted for one 500 mg tablet of Amoxicillin and Clavulanate Potassium. Since both the 250 mg and 500 mg tablets of Amoxicillin and Clavulanate Potassium contain the same amount of clavulanic acid (125 mg, as the potassium salt), two 250 mg tablets of Amoxicillin and Clavulanate Potassium are not equivalent to one 500 mg tablet of Amoxicillin and Clavulanate Potassium.

4 CONTRAINDICATIONS

4.1 Serious Hypersensitivity Reactions

Amoxicillin and Clavulanate Potassium is contraindicated in patients with a history of serious hypersensitivity reactions (e.g., anaphylaxis or Stevens-Johnson syndrome) to amoxicillin, clavulanate or to other beta‑lactam antibacterial drugs (e.g., penicillins and cephalosporins).

4.2 Cholestatic Jaundice/Hepatic Dysfunction

Amoxicillin and Clavulanate Potassium is contraindicated in patients with a previous history of cholestatic jaundice/hepatic dysfunction associated with Amoxicillin and Clavulanate Potassium.

5 WARNINGS AND PRECAUTIONS

5.1 Hypersensitivity Reactions

Serious and occasionally fatal hypersensitivity (anaphylactic) reactions have been reported in patients receiving beta-lactam antibacterials, including Amoxicillin and Clavulanate Potassium. These reactions are more likely to occur in individuals with a history of penicillin hypersensitivity and/or a history of sensitivity to multiple allergens. Before initiating therapy with Amoxicillin and Clavulanate Potassium, careful inquiry should be made regarding previous hypersensitivity reactions to penicillins, cephalosporins, or other allergens. If an allergic reaction occurs, Amoxicillin and Clavulanate Potassium should be discontinued and appropriate therapy instituted.

5.2 Hepatic Dysfunction

Hepatic dysfunction, including hepatitis and cholestatic jaundice has been associated with the use of Amoxicillin and Clavulanate Potassium. Hepatic toxicity is usually reversible; however, deaths have been reported. Hepatic function should be monitored at regular intervals in patients with hepatic impairment.

5.3 Clostridium difficile Associated Diarrhea (CDAD)

Clostridium difficile associated diarrhea (CDAD) has been reported with use of nearly all antibacterial agents, including Amoxicillin and Clavulanate Potassium, and may range in severity from mild diarrhea to fatal colitis. Treatment with antibacterial agents alters the normal flora of the colon leading to overgrowth of C. difficile.

C. difficile produces toxins A and B which contribute to the development of CDAD. Hypertoxin-producing strains of C. difficile cause increased morbidity and mortality, as these infections can be refractory to antimicrobial therapy and may require colectomy. CDAD must be considered in all patients who present with diarrhea following antibacterial use. Careful medical history is necessary since CDAD has been reported to occur over 2 months after the administration of antibacterial agents.

If CDAD is suspected or confirmed, ongoing antibacterial use not directed against C. difficile may need to be discontinued. Appropriate fluid and electrolyte management, protein supplementation, antibacterial treatment of C. difficile, and surgical evaluation should be instituted as clinically indicated.

5.4 Skin Rash in Patients with Mononucleosis

A high percentage of patients with mononucleosis who receive amoxicillin develop an erythematous skin rash. Thus, Amoxicillin and Clavulanate Potassium should not be administered to patients with mononucleosis.

5.5 Potential for Microbial Overgrowth

The possibility of superinfections with fungal or bacterial pathogens should be considered during therapy. If superinfection occurs, amoxicillin/clavulanate potassium should be discontinued and appropriate therapy instituted.

5.6 Phenylketonurics

Amoxicillin and Clavulanate Potassium Chewable tablets and Amoxicillin and Clavulanate Potassium Powder for Oral Solution contain aspartame which contains phenylalanine. Each 200-mg chewable tablet of Amoxicillin and Clavulanate Potassium contains 2.1 mg phenylalanine; each 400-mg chewable tablet contains 4.2 mg phenylalanine; each 5 mL of either the 200 mg/5 mL or 400 mg/5 mL oral suspension contains 7 mg phenylalanine. The other formulations of Amoxicillin and Clavulanate Potassium do not contain phenylalanine.

5.7 Development of Drug-Resistant Bacteria

Prescribing Amoxicillin and Clavulanate Potassium in the absence of a proven or strongly suspected bacterial infection is unlikely to provide benefit to the patient, and increases the risk of the development of drug‑resistant bacteria.

6 ADVERSE REACTIONS

The following are discussed in more detail in other sections of the labeling:

- Anaphylactic reactions [see Warnings and Precautions (5.1) ]
- Hepatic Dysfunction [see Warnings and Precautions (5.2) ]
- CDAD [see Warnings and Precautions (5.3) ]

6.1 Clinical Trial Experience

Because clinical trials are conducted under widely varying conditions, adverse reaction rates observed in the clinical trials of a drug cannot be directly compared to rates in the clinical trials of another drug and may not reflect the rates observed in practice.

The most frequently reported adverse reactions were diarrhea/loose stools (9%), nausea (3%), skin rashes and urticaria (3%), vomiting (1%) and vaginitis (1%). Less than 3% of patients discontinued therapy because of drug‑related adverse reactions. The overall incidence of adverse reactions, and in particular diarrhea, increased with the higher recommended dose. Other less frequently reported adverse reactions (<1%) include: Abdominal discomfort, flatulence, and headache.

In pediatric patients (aged 2 months to 12 years), 1 US/Canadian clinical trial was conducted which compared 45/6.4 mg/kg/day (divided every 12 hours) of Amoxicillin and Clavulanate Potassium for 10 days versus 40/10 mg/kg/day (divided every 8 hours) of Amoxicillin and Clavulanate Potassium for 10 days in the treatment of acute otitis media. A total of 575 patients were enrolled, and only the suspension formulations were used in this trial. Overall, the adverse reactions seen were comparable to that noted above; however, there were differences in the rates of diarrhea, skin rashes/urticaria, and diaper area rashes. [See Clinical Studies (14.2)]

6.2 Postmarketing Experience

In addition to adverse reactions reported from clinical trials, the following have been identified during postmarketing use of Amoxicillin and Clavulanate Potassium. Because they are reported voluntarily from a population of unknown size, estimates of frequency cannot be made. These events have been chosen for inclusion due to a combination of their seriousness, frequency of reporting, or potential causal connection to Amoxicillin and Clavulanate Potassium.

Gastrointestinal: Indigestion, gastritis, stomatitis, glossitis, black “hairy” tongue, mucocutaneous candidiasis, enterocolitis, and hemorrhagic/pseudomembranous colitis. Onset of pseudomembranous colitis symptoms may occur during or after antibiotic treatment. [see Warnings and Precautions (5.3) ]

Hypersensitivity Reactions: Pruritus, angioedema, serum sickness–like reactions (urticaria or skin rash accompanied by arthritis, arthralgia, myalgia, and frequently fever), erythema multiforme, Stevens‑Johnson syndrome, acute generalized exanthematouspustulosis, hypersensitivity vasculitis, and cases of exfoliative dermatitis (including toxic epidermal necrolysis) have been reported. [see Warnings and Precautions (5.1) ]

Liver: Hepatic dysfunction, including hepatitis and cholestatic jaundice, increases in serum transaminases (AST and/or ALT), serum bilirubin, and/or alkaline phosphatase, has been reported with Amoxicillin and Clavulanate Potassium. It has been reported more commonly in the elderly, in males, or in patients on prolonged treatment. The histologic findings on liver biopsy have consisted of predominantly cholestatic, hepatocellular, or mixed cholestatic‑hepatocellular changes. The onset of signs/symptoms of hepatic dysfunction may occur during or several weeks after therapy has been discontinued. The hepatic dysfunction, which may be severe, is usually reversible. Deaths have been reported. [see Contraindications (4.2), Warnings and Precautions (5.2) ]

Renal:Interstitial nephritis, hematuria, and crystalluria have been reported. [see Overdosage (10) ]

Hemic and Lymphatic Systems: Anemia, including hemolytic anemia, thrombocytopenia, thrombocytopenic purpura, eosinophilia, leukopenia, and agranulocytosishave been reported. These reactions are usually reversible on discontinuation of therapy and are believed to be hypersensitivity phenomena. Thrombocytosis was noted in less than 1% of the patients treated with Amoxicillin and Clavulanate Potassium. There have been reports of increased prothrombin time in patients receiving Amoxicillin and Clavulanate Potassium and anticoagulant therapy concomitantly. [see Drug Interactions (7.2) ]

Central Nervous System: Agitation, anxiety, behavioral changes, confusion, convulsions, dizziness, insomnia, and reversible hyperactivity have been reported.

Miscellaneous: Tooth discoloration (brown, yellow, or gray staining) has been reported. Most reports occurred in pediatric patients. Discoloration was reduced or eliminated with brushing or dental cleaning in most cases.

7 DRUG INTERACTIONS

7.1 Probenecid

Probenecid decreases the renal tubular secretion of amoxicillin but does not delay renal excretion of clavulanic acid. Concurrent use with Amoxicillin and Clavulanate Potassium may result in increased and prolonged blood concentrations of amoxicillin. Coadministration of probenecid is not recommended.

7.2 Oral Anticoagulants

Abnormal prolongation of prothrombin time (increased international normalized ratio [INR]) has been reported in patients receiving amoxicillin and oral anticoagulants. Appropriate monitoring should be undertaken when anticoagulants are prescribed concurrently with Amoxicillin and Clavulanate Potassium. Adjustments in the dose of oral anticoagulants may be necessary to maintain the desired level of anticoagulation.

7.3 Allopurinol

The concurrent administration of allopurinol and amoxicillin increases the incidence of rashes in patients receiving both drugs as compared to patients receiving amoxicillin alone. It is not known whether this potentiation of amoxicillin rashes is due to allopurinol or the hyperuricemia present in these patients.

7.4 Oral Contraceptives

Amoxicillin and Clavulanate Potassium may affect intestinal flora, leading to lower estrogen reabsorption and reduced efficacy of combined oral estrogen/progesterone contraceptives.

7.5 Effects on Laboratory Tests

High urine concentrations of amoxicillin may result in false-positive reactions when testing for the presence of glucose in urine using CLINITEST®, Benedict’s Solution, or Fehling’s Solution. Since this effect may also occur with Amoxicillin and Clavulanate Potassium, it is recommended that glucose tests based on enzymatic glucose oxidase reactions be used.

Following administration of amoxicillin to pregnant women, a transient decrease in plasma concentration of total conjugated estriol, estriol-glucuronide, conjugated estrone, and estradiol has been noted.

8 USE IN SPECIFIC POPULATIONS

8.1 Pregnancy

Teratogenic Effects:Pregnancy Category B. Reproduction studies performed in pregnant rats and mice given Amoxicillin and Clavulanate Potassium (2:1 ratio formulation of amoxicillin:clavulanate) at oral doses up to 1200 mg/kg/day revealed no evidence of harm to the fetus due to Amoxicillin and Clavulanate Potassium. The amoxicillin doses in rats and mice (based on body surface area) were approximately 4 and 2 times the maximum recommended adult human oral dose (875 mg every 12 hours). For clavulanate, these dose multiples were approximately 9 and 4 times the maximum recommended adult human oral dose (125 mg every 8 hours). There are, however, no adequate and well-controlled studies in pregnant women. Because animal reproduction studies are not always predictive of human response, this drug should be used during pregnancy only if clearly needed.

8.2 Labor and Delivery

Oral ampicillin‑class antibiotics are poorly absorbed during labor. It is not known whether use of amoxicillin/clavulanate potassium in humans during labor or delivery has immediate or delayed adverse effects on the fetus, prolongs the duration of labor, or increases the likelihood of the necessity for an obstetrical intervention.

8.3 Nursing Mothers

Amoxicillin has been shown to be excreted in human milk. Amoxicillin/clavulanate potassium use by nursing mothers may lead to sensitization of infants. Caution should be exercised when amoxicillin/clavulanate potassium is administered to a nursing woman.

8.4 Pediatric Use

The safety and effectiveness of Amoxicillin and Clavulanate Potassium Powder for Oral Suspension and Chewable Tablets have been established in pediatric patients. Use of Amoxicillin and Clavulanate Potassium in pediatric patients is supported by evidence from studies of Amoxicillin and Clavulanate Potassium Tablets in adults with additional data from a study of Amoxicillin and Clavulanate Potassium Powder for Oral Suspension in pediatric patients aged 2 months to 12 years with acute otitis media. [see Clinical Studies (14.2)]

Because of incompletely developed renal function in neonates and young infants, the elimination of amoxicillin may be delayed; clavulanate elimination is unaltered in this age group. Dosing of Amoxicillin and Clavulanate Potassium should be modified in pediatric patients aged <12 weeks (<3 months). [see Dosage and Administration (2.2)]

8.5 Geriatric Use

Of the 3,119 patients in an analysis of clinical studies of Amoxicillin and Clavulanate Potassium, 32% were ≥65 years old, and 14% were ≥75 years old. No overall differences in safety or effectiveness were observed between these subjects and younger subjects, and other reported clinical experience has not identified differences in responses between the elderly and younger patients, but greater sensitivity of some older individuals cannot be ruled out.

This drug is known to be substantially excreted by the kidney, and the risk of adverse reactions to this drug may be greater in patients with impaired renal function. Because elderly patients are more likely to have decreased renal function, care should be taken in dose selection, and it may be useful to monitor renal function.

8.6 Dosing in Renal Impairment

Amoxicillin is primarily eliminated by the kidney and dosage adjustment is usually required in patients with severe renal impairment (GFR <30 mL/min). See Patients with Renal Impairment (2.3) for specific recommendations in patients with renal impairment.

10 OVERDOSAGE

In case of overdosage, discontinue medication, treat symptomatically, and institute supportive measures as required. A prospective study of 51 pediatric patients at a poison-control center suggested that overdosages of less than 250 mg/kg of amoxicillin are not associated with significant clinical symptoms^1.

Interstitial nephritis resulting in oliguric renal failure has been reported in patients after overdosage with amoxicillin/clavulanate potassium.

Crystalluria, in some cases leading to renal failure, has also been reported after amoxicillin/clavulanate potassium overdosage in adult and pediatric patients. In case of overdosage, adequate fluid intake and diuresis should be maintained to reduce the risk of amoxicillin/clavulanate potassium crystalluria.

Renal impairment appears to be reversible with cessation of drug administration. High blood levels may occur more readily in patients with impaired renal function because of decreased renal clearance of amoxicillin/clavulanate potassium. Amoxicillin/clavulanate potassium may be removed from circulation by hemodialysis. [see Dosage and Administration (2.3)]

11 DESCRIPTION

Amoxicillin and Clavulanate Potassium is an oral antibacterial combination consisting of amoxicillin and the beta‑lactamase inhibitor, clavulanate potassium (the potassium salt of clavulanic acid). Amoxicillin is an analog of ampicillin, derived from the basic penicillin nucleus, 6‑aminopenicillanic acid. The amoxicillin molecular formula is C16H19N3O5S•3H2O, and the molecular weight is 419.46. Chemically, amoxicillin is (2S,5R,6R)-6-[(R)-(-)-2-Amino-2-(p-hydroxyphenyl)acetamido]-3,3-dimethyl-7-oxo-4-thia-1-azabicyclo[3.2.0]heptane-2-carboxylic acid trihydrate and may be represented structurally as:

Clavulanic acid is produced by the fermentation of Streptomyces clavuligerus. It is a beta-lactam structurally related to the penicillins and possesses the ability to inactivate some beta‑lactamases by blocking the active sites of these enzymes. The clavulanate potassium molecular formula is C8H8KNO5, and the molecular weight is 237.25. Chemically, clavulanate potassium is potassium (Z)(2R,5R)-3-(2-hydroxyethylidene)-7-oxo-4-oxa-1-azabicyclo[3.2.0]-heptane-2-carboxylate and may be represented structurally as:

Inactive Ingredients:

- Tablets- Colloidal silicon dioxide, hypromellose, magnesium stearate, microcrystalline cellulose, polyethylene glycol, sodium starch glycolate, and titanium dioxide. Each tablet of amoxicillin/clavulanate potassium contains 0.63 mEq potassium.
- Powder for Oral Suspension- Colloidal silicon dioxide, flavorings, xanthan gum, and one or more of the following: hypromellose, mannitol, silica gel, silicon dioxide, succinic acid, sodium saccharin, and aspartame. [see Warnings and Precautions (5.6)]
- Chewable Tablets- Colloidal silicon dioxide, flavorings, magnesium stearate, mannitol, and one or more of the following: D&C Yellow No. 10, FD&C Red No. 40, glycine, sodium saccharin, and aspartame. [see Warnings and Precautions (5.6)]
  - Each 125-mg chewable tablet and each 5 mL of reconstituted 125/5 mL oral suspension of Amoxicillin and Clavulanate Potassium contains 0.16 mEq potassium
  - Each 250-mg chewable tablet and each 5 mL of reconstituted 250/5 mL oral suspension of Amoxicillin and Clavulanate Potassium contains 0.32 mEq potassium
  - Each 200-mg chewable tablet and each 5 mL of reconstituted 200/5 mL oral suspension of Amoxicillin and Clavulanate Potassium contains 0.14 mEq potassium
  - Each 400-mg chewable tablet and each 5 mL of reconstituted 400/5 mL oral suspension of Amoxicillin and Clavulanate Potassium contains 0.29 mEq potassium

12 CLINICAL PHARMACOLOGY

12.1 Mechanism of Action

Amoxicillin and Clavulanate Potassium is an antibacterial drug. [see Microbiology 12.4]

12.3 Pharmacokinetics

Mean amoxicillin and clavulanate potassium pharmacokinetic parameters in normal adults following administration of Amoxicillin and Clavulanate Potassium Tablets are shown in Table 3 and following administration of Amoxicillin and Clavulanate Potassium Powder for Oral Suspension and Chewable Tablets are shown in Table 4.

Table 3: Mean (±S.D.) Amoxicillin and Clavulanate Potassium Pharmacokinetic Parametersa,b with Amoxicillin and Clavulanate Potassium Tablets

Dose and Regimen | Cmax (mcg/mL) |  | AUC0-24 (mcg*h/mL)
Amoxicillin/Clavulanate potassium | Amoxicillin | Clavulanate potassium | Amoxicillin | Clavulanate potassium
250/125 mg every 8 hours | 3.3 ± 1.12 | 1.5 ± 0.70 | 26.7 ± 4.56 | 12.6 ± 3.25
500/125 mg every 12 hours | 6.5 ± 1.41 | 1.8 ± 0.61 | 33.4 ± 6.76 | 8.6 ± 1.95
500 125 mg every 8 hours | 7.2 ± 2.26 | 2.4 ± 0.83 | 53.4 ± 8.87 | 15.7 ± 3.86
875/125 mg every 12 hours | 11.6 ± 2.78 | 2.2 ± 0.99 | 53.5 ± 12.31 | 10.2 ± 3.04

a Mean (± standard deviation) values of 14 normal adults (N=15 for clavulanate potassium in the low-dose regimens). Peak concentrations occurred approximately 1.5 hours after the dose.

b Amoxicillin/clavulanate potassium administered at the start of a light meal.

Table 4: Mean (±S.D.) Amoxicillin and Clavulanate Potassium Pharmacokinetic Parametersa,b with Amoxicillin and Clavulanate Potassium Powder for Oral Suspension and Chewable Tablets

Dose | Cmax (mcg/mL) |  | AUC0-24 (mcg*h/mL)
Amoxicillin/Clavulanate potassium | Amoxicillin | Clavulanate potassium | Amoxicillin | Clavulanate potassium
400/57 mg(5 mL of suspension) | 6.94 ± 1.24 | 1.10 ± 0.42 | 17.29 ± 2.28 | 2.34 ± 0.94
400/57 mg(1 chewable tablet) | 6.67 ± 1.37 | 1.03 ± 0.33 | 17.24 ± 2.64 | 2.17 ± 0.73

a Mean (± standard deviation) values of 28 normal adults. Peak concentrations occurred approximately 1 hour after the dose.

b Amoxicillin/clavulanate potassium administered at the start of a light meal.

Oral administration of 5 mL of 250 mg/5 mL suspension of Amoxicillin and Clavulanate Potassium or the equivalent dose of 10 mL of 125 mg/5 mL suspension of Amoxicillin and Clavulanate Potassium provides average peak serum concentrations approximately 1 hour after dosing of 6.9 mcg/mL for amoxicillin and 1.6 mcg/mL for clavulanic acid. The areas under the serum concentration curves obtained during the first 4 hours after dosing were 12.6 mcg*h/mL for amoxicillin and 2.9 mcg*h/mL for clavulanic acid when 5 mL of 250 mg/5 mL suspension of Amoxicillin and Clavulanate Potassium or equivalent dose of 10 mL of 125 mg/5 mL suspension of Amoxicillin and Clavulanate Potassium were administered to normal adults. One 250-mg chewable tablet of Amoxicillin and Clavulanate Potassium or two 125-mg chewable tablets of Amoxicillin and Clavulanate Potassium are equivalent to 5 mL of 250 mg/5 mL suspension of Amoxicillin and Clavulanate Potassium and provide similar serum concentrations of amoxicillin and clavulanic acid.

Amoxicillin serum concentrations achieved with Amoxicillin and Clavulanate Potassium are similar to those produced by the oral administration of equivalent doses of amoxicillin alone. Time above the minimum inhibitory concentration of 1 mcg/mL for amoxicillin has been shown to be similar after corresponding every 12 hour and every 8 hour dosing regimens of Amoxicillin and Clavulanate Potassium in adults and children.

Absorption: Dosing in the fasted or fed state has minimal effect on the pharmacokinetics of amoxicillin. While Amoxicillin and Clavulanate Potassium can be given without regard to meals, absorption of clavulanate potassium when taken with food is greater relative to the fasted state. In one study, the relative bioavailability of clavulanate was reduced when Amoxicillin and Clavulanate Potassium was dosed at 30 and 150 minutes after the start of a high‑fat breakfast.

Distribution: Neither component in Amoxicillin and Clavulanate Potassium is highly protein‑bound; clavulanic acid is approximately 25% bound to human serum and amoxicillin approximately 18% bound.

Amoxicillin diffuses readily into most body tissues and fluids with the exception of the brain and spinal fluid.

Two hours after oral administration of a single 35 mg/kg dose of suspension of Amoxicillin and Clavulanate Potassium to fasting children, average concentrations of 3 mcg/mL of amoxicillin and 0.5 mcg/mL of clavulanic acid were detected in middle ear effusions.

Metabolism and Excretion: The half‑life of amoxicillin after the oral administration of Amoxicillin and Clavulanate Potassium is 1.3 hours and that of clavulanic acid is 1 hour.

Approximately 50% to 70% of the amoxicillin and approximately 25% to 40% of the clavulanic acid are excreted unchanged in urine during the first 6 hours after administration of a single 250‑mg or 500‑mg tablet of Amoxicillin and Clavulanate Potassium.

12.4 Microbiology

Amoxicillin is a semisynthetic antibiotic with in vitro bactericidal activity against Gram-positive and Gram-negative bacteria. Amoxicillin is, however, susceptible to degradation by beta-lactamases, and therefore, the spectrum of activity does not include organisms which produce these enzymes. Clavulanic acid is a beta-lactam, structurally related to the penicillins, which possesses the ability to inactivate some beta-lactamase enzymes commonly found in microorganisms resistant to penicillins and cephalosporins. In particular, it has good activity against the clinically important plasmid-mediated beta-lactamases frequently responsible for transferred drug resistance.

The formulation of amoxicillin and clavulanic acid in Amoxicillin and Clavulanate Potassium protects amoxicillin from degradation by some beta-lactamase enzymes and extends the antibiotic spectrum of amoxicillin to include many bacteria normally resistant to amoxicillin.

Amoxicillin/clavulanic acid has been shown to be active against most isolates of the following bacteria, both in vitro and in clinical infections as described in the INDICATIONS AND USAGE section.

Gram-positive bacteria

Staphylococcus aureus

Gram-negative bacteria

Enterobacter species

Escherichia coli

Haemophilus influenzae

Klebsiella species

Moraxella catarrhalis

The following in vitro data are available, but their clinical significance is unknown. At least 90 percent of the following bacteria exhibit an in vitro minimum inhibitory concentration (MIC) less than or equal to the susceptible breakpoint for amoxicillin/clavulanic acid. However, the efficacy of amoxicillin/clavulanic acid in treating clinical infections due to these bacteria has not been established in adequate and well-controlled clinical trials.

Gram-positive bacteria

Enterococcus faecalis

Staphylococcus epidermidis

Staphylococcus saprophyticus

Streptococcus pneumoniae

Streptococcus pyogenes

Viridans group Streptococcus

Gram-negative Bacteria

Eikenellacorrodens

Proteus mirabilis

Anaerobic Bacteria

Bacteroidesspecies including Bacteroides fragilis

Fusobacterium species

Peptostreptococcus species

Susceptibility Test Methods

When available, the clinical microbiology laboratory should provide the results of in vitro susceptibility test results for antimicrobial drug products used in resident hospitals to the physician as periodic reports that describe the susceptibility profile of nosocomial and community-acquired pathogens. These reports should aid the physician in selecting an antibacterial drug product for treatment.

Dilution techniques

Quantitative methods are used to determine antimicrobial minimum inhibitory concentrations (MICs). These MICs provide estimates of the susceptibility of bacteria to antimicrobial compounds. The MICs should be determined using a standardized test method^2,3 (broth and/or agar). The MIC values should be interpreted according to criteria provided in Table 5.

Diffusion techniques:

Quantitative methods that require measurement of zone diameters can also provide reproducible estimates of the susceptibility of bacteria to antimicrobial compounds. The zone size provides an estimate of the susceptibility of bacteria to antimicrobial compounds. The zone size should be determined using a standardized test method^3,4. This procedure uses paper disks impregnated with 30 mcg amoxicillin/clavulanic acid (20 mcg amoxicillin plus 10 mcg clavulanic acid) to test the susceptibility of bacteria to amoxicillin/clavulanic acid. The disc diffusion interpretive criteria are provided in Table 5.

Table 5:Susceptibility Test Interpretive Criteria for Amoxicillin Clavulanic Acid

Minimum Inhibitory Concentrations (mcg/mL) |  | Disk Diffusion (zone diameters in mm)
Pathogen | S | I | R | S | I | R
Enterobacteriaceae | 8/4 | 16/8 | 32/16 | >18 | 14-17 | ≥13
Haemophilus influenzae and Staphylococcus aureus | 4/2 | -- | 8/4 | >20 | -- | ≤19

Quality Control:

Standardized susceptibility test procedures require the use of laboratory controls to monitor and ensure the accuracy and precision of supplies and reagents used in the assay, and the techniques of the individuals performing the test^2,3,4. Standard amoxicillin/clavulanic acid powder should provide the following range of MIC values noted in Table 6 for the diffusion technique using the 30 mcg amoxicillin/clavulanic acid (20 mcg amoxicillin plus 10 mcg clavulanic acid) disk, the criteria in Table 6 should be achieved.

Table 6: Acceptable Quality Control Ranges for Amoxicillin/Clavulanic Acid

QC Strain | Minimum Inhibitory Concentration (mcg/mL) | Disk Diffusion(zone diameter in mm)
Escherichia coli ATCC 25922 | 2/1 to 8/4 | 18 to 24
Escherichia coli ATCC 35218 | 4/2 to 16/8 | 17 to 22
Haemophilus influenzae ATCC 49247 | 2/1 to 16/8 | 15 to 23
Staphylococcus aureus ATCC 29213 | 0.12/0.06 to 0.5/0.25 | --
Staphylococcus aureus ATCC 29523 | -- | 28 to 36

13 NONCLINICAL TOXICOLOGY

13.1 Carcinogenesis, Mutagenesis, Impairment Of Fertility

Long‑term studies in animals have not been performed to evaluate carcinogenic potential.

Amoxicillin and Clavulanate Potassium (4:1 ratio formulation of amoxicillin:clavulanate) was non-mutagenic in the Ames bacterial mutation assay, and the yeast gene conversion assay. Amoxicillin and Clavulanate Potassium was weakly positive in the mouse lymphoma assay, but the trend toward increased mutation frequencies in this assay occurred at doses that were also associated with decreased cell survival. Amoxicillin and Clavulanate Potassium was negative in the mouse micronucleus test, and in the dominant lethal assay in mice. Potassium clavulanate alone was tested in the Ames bacterial mutation assay and in the mouse micronucleus test, and was negative in each of these assays.

Amoxicillin and Clavulanate Potassium (2:1 ratio formulation of amoxicillin:clavulanate) at oral doses of up to 1,200 mg/kg/day was found to have no effect on fertility and reproductive performance in rats. Based on body surface area, this dose of amoxicillin is approximately 4 times the maximum recommended adult human oral dose (875 mg every 12 hours). For clavulanate, the dose multiple is approximately 9 times higher than the maximum recommended adult human oral dose (125 mg every 8 hours), also based on body surface area.

14 CLINICAL STUDIES

14.1 Lower Respiratory Tract and Complicated Urinary Tract Infections

Data from 2 pivotal trials in 1,191 patients treated for either lower respiratory tract infections or complicated urinary tract infections compared a regimen of 875‑mg tablets of Amoxicillin and Clavulanate Potassium every 12 hours to 500‑mg tablets of Amoxicillin and Clavulanate Potassium dosed every 8 hours (584 and 607 patients, respectively). Comparable efficacy was demonstrated between the every 12 hours and every 8 hours dosing regimens. There was no significant difference in the percentage of adverse events in each group. The most frequently reported adverse event was diarrhea; incidence rates were similar for the 875‑mg every 12 hours and 500‑mg every 8 hours dosing regimens (15% and 14%, respectively); however, there was a statistically significant difference (p < 0.05) in rates of severe diarrhea or withdrawals with diarrhea between the regimens: 1% for 875‑mg every 12 hours regimen versus 2% for the 500‑mg every 8 hours regimen.

In one of these pivotal trials, patients with either pyelonephritis (n = 361) or a complicated urinary tract infection (i.e., patients with abnormalities of the urinary tract that predispose to relapse of bacteriuria following eradication, n = 268) were randomized (1:1) to receive either 875‑mg tablets of Amoxicillin and Clavulanate Potassium every 12 hours (n=308) or 500‑mg tablets of Amoxicillin and Clavulanate Potassium every 8 hours (n=321).

The number of bacteriologically evaluable patients was comparable between the two dosing regimens. Amoxicillin and Clavulanate Potassium produced comparable bacteriological success rates in patients assessed 2 to 4 days immediately following end of therapy. The bacteriologic efficacy rates were comparable at one of the follow‑up visits (5 to 9 days post‑therapy) and at a late post‑therapy visit (in the majority of cases, this was 2 to 4 weeks post-therapy), as seen in Table 7.

Table 7: Bacteriologic efficacy rates for Amoxicillin and Clavulanate Potassium

Time Post Therapy | 875 mg every 12 hours% (n) | 500 mg every 8 hours% (n)
2 to 4 days | 81% (58) | 80% (54)
5 to 9 days | 58% (41) | 52% (52)
2 to 4 weeks | 52% (101) | 55% (104)

As noted before, though there was no significant difference in the percentage of adverse events in each group, there was a statistically significant difference in rates of severe diarrhea or withdrawals with diarrhea between the regimens.

14.2 Acute Bacterial Otitis Media and Diarrhea in Pediatric Patients

One US/Canadian clinical trial was conducted which compared 45/6.4 mg/kg/day (divided every 12 hours) of Amoxicillin and Clavulanate Potassium for 10 days versus 40/10 mg/kg/day (divided every 8 hours) of Amoxicillin and Clavulanate Potassium for 10 days in the treatment of acute otitis media. Only the suspension formulations were used in this trial. A total of 575 pediatric patients (aged 2 months to 12 years) were enrolled, with an even distribution among the 2 treatment groups and a comparable number of patients were evaluable (i.e., ≥ 84%) per treatment group. Otitis media‑specific criteria were required for eligibility and a strong correlation was found at the end of therapy and follow‑up between these criteria and physician assessment of clinical response. The clinical efficacy rates at the end of therapy visit (defined as 2‑4 days after the completion of therapy) and at the follow‑up visit (defined as 22‑28 days post‑completion of therapy) were comparable for the 2 treatment groups, with the following cure rates obtained for the evaluable patients: At end of therapy, 87% (n = 265) and 82% (n = 260) for 45 mg/kg/day every 12 hours and 40 mg/kg/day every 8 hours, respectively. At follow‑up, 67% (n = 249) and 69% (n = 243) for 45 mg/kg/day every 12 hours and 40 mg/kg/day every 8 hours, respectively.

Diarrhea was defined as either: (a) 3 or more watery or 4 or more loose/watery stools in 1 day; OR (b) 2 watery stools per day or 3 loose/watery stools per day for 2 consecutive days. The incidence of diarrhea was significantly lower in patients who received the every 12 hours regimen compared to patients who received the every 8 hours regimen (14% and 34%, respectively). In addition, the number of patients with either severe diarrhea or who were withdrawn with diarrhea was significantly lower in the every 12 hours treatment group (3% and 8% for the every 12 hours/10 day and every 8 hours/10 day, respectively). In the every 12 hours treatment group, 3 patients (1%) were withdrawn with an allergic reaction, while 1 patient in the every 8 hours group was withdrawn for this reason. The number of patients with a candidal infection of the diaper area was 4% and 6% for the every 12 hours and every 8 hours groups, respectively.

It is not known if the finding of a statistically significant reduction in diarrhea with the oral suspensions dosed every 12 hours, versus suspensions dosed every 8 hours, can be extrapolated to the chewable tablets. The presence of mannitol in the chewable tablets may contribute to a different diarrhea profile. The every 12 hour oral suspensions (200 mg/5 mL and 400 mg/5 mL) are sweetened with aspartame.

15 REFERENCES

1. Swanson-Biearman B, Dean BS, Lopez G, Krenzelok EP. The effects of penicillin and cephalosporin ingestions in children less than six years of age.Vet Hum Toxicol. 1988; 30: 66‑67.

2. Clinical and Laboratory Standards Institute (CLSI). Methods for Dilution Antimicrobial Susceptibility Tests for Bacteria that Grow Aerobically; Approved Standard – 8th ed. CLSI Document M7-A9. CLSI, 940 West Valley Road, Suite 1400, Wayne, PA, 19087, 2012.

3. Clinical and Laboratory Standards Institute (CLSI). Performance Standard for Antimicrobial Disk Susceptibility Tests;Approved Standard – 11th ed. CLSI Document M2-A11. CLSI, 940 West Valley Road, Suite 1400, Wayne, PA, 19087, 2012.

4. CLSI. Performance Standards for Antimicrobial Susceptibility Testing: 22nd Informational Supplement. CLSI document M100-S22. CLSI, Wayne, PA, 2012.

16 HOW SUPPLIED/STORAGE AND HANDLING

Powder for Oral Suspension:

Amoxicillin and Clavulanate Potassium 400 mg/57 mg per 5 mL for OralSuspension: Each 5 mL of reconstituted orange-flavored suspension contains 400 mgamoxicillin and 57 mg clavulanic acid as the potassium salt.

NDC 43598-208-50 ..............50 mL bottle

NDC 43598-208-51 ..............75 mL bottle

NDC 43598-208-52 ............. 100 mL bottle

NDC 43598-216-31 carton of 30 tablets

Store tablets and dry powder at or below 25°C (77°F).

Dispense in original containers.

Store reconstituted suspension under refrigeration.

Discard unused suspension after 10 days.

CLINITEST is a registered trademark of Miles, Inc.

Distributed by:

Dr. Reddy’s Laboratories Inc.

Bridgewater, NJ 08807

Relabeled by:

Proficient Rx LP

Thousand Oaks, CA 91320

17 PATIENT COUNSELING INFORMATION

17.1 INFORMATION FOR PATIENTS

Patients should be informed that Amoxicillin and Clavulanate Potassium may be taken every 8 hours or every 12 hours, depending on the dose prescribed. Each dose should be taken with a meal or snack to reduce the possibility of gastrointestinal upset.

Patients should be counseled that antibacterial drugs, including Amoxicillin and Clavulante Potassium, should only be used to treat bacterial infections. They do not treat viral infections (e.g., the common cold). When Amoxicillin and Clavulante Potassium is prescribed to treat a bacterial infection, patients should be told that although it is common to feel better early in the course of therapy, the medication should be taken exactly as directed. Skipping doses or not completing the full course of therapy may: (1) decrease the effectiveness of the immediate treatment, and (2) increase the likelihood that bacteria will develop resistance and will not be treatable by Amoxicillin and Clavulante Potassium or other antibacterial drugs in the future.

Counsel patients that diarrhea is a common problem caused by antibacterials, and it usually ends when the antibacterial is discontinued. Sometimes after starting treatment with antibacterials, patients can develop watery and bloody stools (with or without stomach cramps and fever) even as late as 2 or more months after having taken their last dose of the antibacterial. If diarrhea is severe or lasts more than 2 or 3 days, patients should contact their physician.

Patients should be advised to keep suspension refrigerated. Shake well before using. When dosing a child with the suspension (liquid) of Amoxicillin and Clavulante Potassium, use a dosing spoon or medicine dropper. Be sure to rinse the spoon or dropper after each use. Bottles of suspension of Amoxicillin and Clavulante Potassium may contain more liquid than required. Follow your doctor’s instructions about the amount to use and the days of treatment your child requires. Discard any unused medicine.

Patients should be aware that Amoxicillin and Clavulante Potassium contains a penicillin class drug product that can cause allergic reactions in some individuals.

PRINCIPAL DISPLAY PANEL

NDC 63187-320-00

Amoxicillin and Clavulanate Potassium

400 mg/57 mg per 5 mL

AMOXICILLIN/CLAVULANATE POTASSIUM

FOR ORAL SUSPENSION

When reconstituted, each 5 mL contains:

AMOXICILLIN, 400 MG,

as the trihydrate

CLAVULANIC ACID, 57 MG,

as clavulanate potassium

75 mL (when reconstituted)

Rx only

Directions for mixing:

Tap bottle until all powder flows freely. Add approximately 2/3 of total water for reconstitution (total = 70 mL); shake vigorously to wet powder. Add remaining water; again shake vigorously.

Dosage: Administer every 12 hours. See accompanying prescribing information.

Phenylketonurics: Contains phenylalanine 7 mg per 5 mL.Keep tightly closed.

Shake well before using.

Must be refrigerated.

Discard after 10 days.

Use only if inner seal is intact.

Net contents: Equivalent to 6 g amoxicillin and 0.855 g clavulanic acid.

Store dry powder at or below room temperature.

Mfd. By: Dr. Reddy's Laboratories Inc.,Bridgewater, NJ 08807

Relabeled by

Proficient Rx LP

Thousand Oaks, CA 91320

I1111

150035374